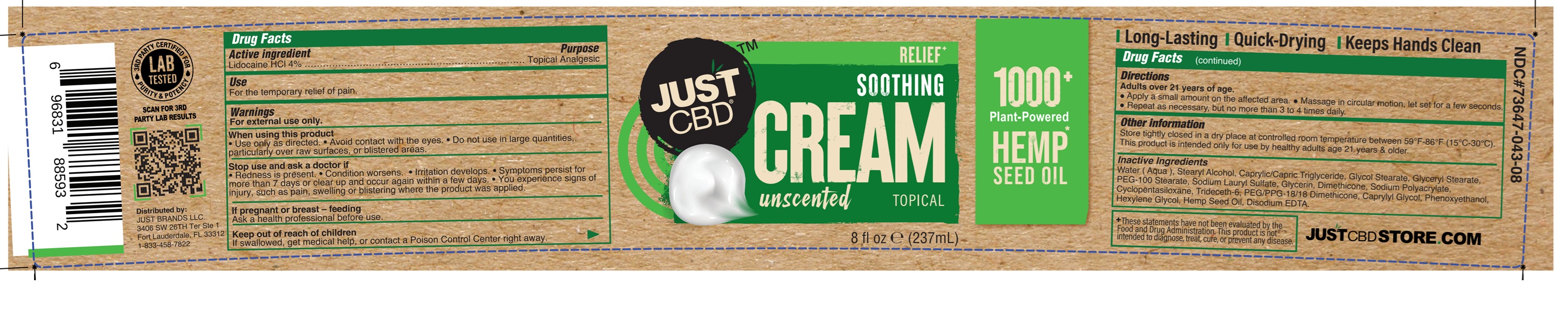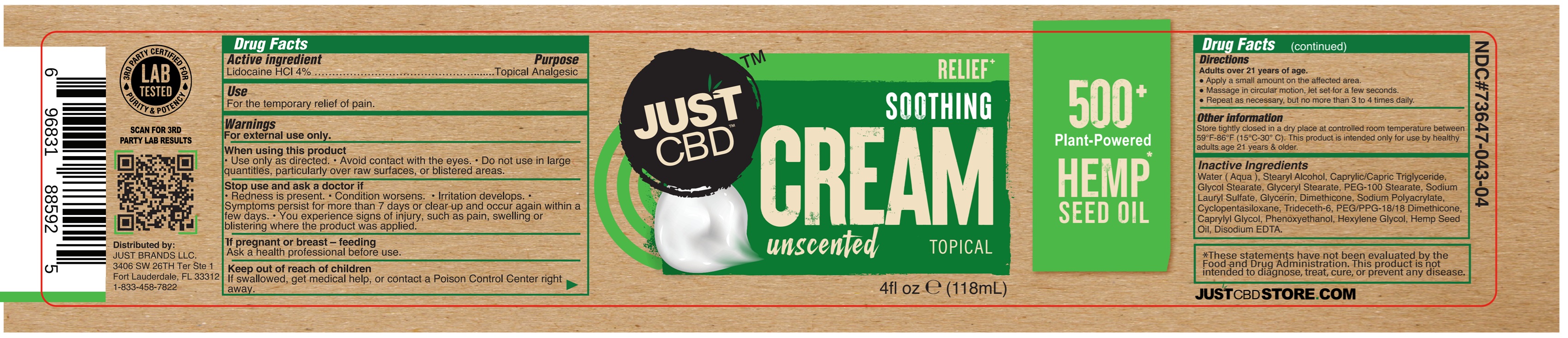 DRUG LABEL: JUST CBD SOOTHING UNSCENTED
NDC: 73647-043 | Form: CREAM
Manufacturer: Just Brands LLC
Category: otc | Type: HUMAN OTC DRUG LABEL
Date: 20251205

ACTIVE INGREDIENTS: LIDOCAINE HYDROCHLORIDE 4 g/100 mL
INACTIVE INGREDIENTS: EDETATE DISODIUM ANHYDROUS; GLYCERIN; CAPRYLYL GLYCOL; PHENOXYETHANOL; GLYCERYL STEARATE/PEG-100 STEARATE; SODIUM LAURYL SULFATE; GLYCOL STEARATE; WATER; STEARYL ALCOHOL; HEXYLENE GLYCOL; CANNABIS SATIVA SEED OIL; MEDIUM-CHAIN TRIGLYCERIDES; TRIDECETH-6; PEG/PPG-18/18 DIMETHICONE; DIMETHICONE 350; CYCLOMETHICONE 5; SODIUM POLYACRYLATE (8000 MW)

73647-043-04
73647-043-08

ACTIVE INGREDIENT

Lidocaine HCl 4%

PURPOSE

Topical Analgesic

Use

For the temporary relief of pain.

WARNINGS

For external use only.

WHEN USING

• Use only as directed. • Avoid contact with the eyes. • Do not use in large quantities, particularly over raw surfaces, or blistered areas.

STOP USE

• Redness is present. • Condition worsens. • Irritation develops. • Symptoms persist for more than 7 days or clear up and occur again within a few days. • You experience signs of injury, such as pain, swelling or blistering where the product was applied.

PREGNANCY OR BREAST FEEDING

Ask a health professional before use.

KEEP OUT OF REACH OF CHILDREN

If swallowed, get medical help, or contact a Poison Control Center right away.

Directions

Adults over 21 years:

• Apply a small amount on the affected area.• Massage in circular motion, let set for a few seconds.• Repeat as necessary, but no more than 3 to 4 times daily

Other information

Store tightly closed in a dry place at controlled room temperature between 59ºF - 86ºF (15 ºC - 30º C).

This product is intended only for use by healthy adults aged 21 years & older.

INACTIVE INGREDIENT

Water (Aqua), Stearyl Alcohol, Caprylic/Capric Triglyceride, Glycol Stearate, Glyceryl Stearate, PEG-100 Stearate, Sodium Lauryl Sulfate, Glycerin, Dimethicone, Sodium Polyacrylate, Cyclopentasiloxane, Trideceth-6, PEG/PPG-18/18 Dimethicone, Caprylyl Glycol, Phenoxyethanol, Hexylene Glycol, Hemp Seed Oil, Disodium EDTA.